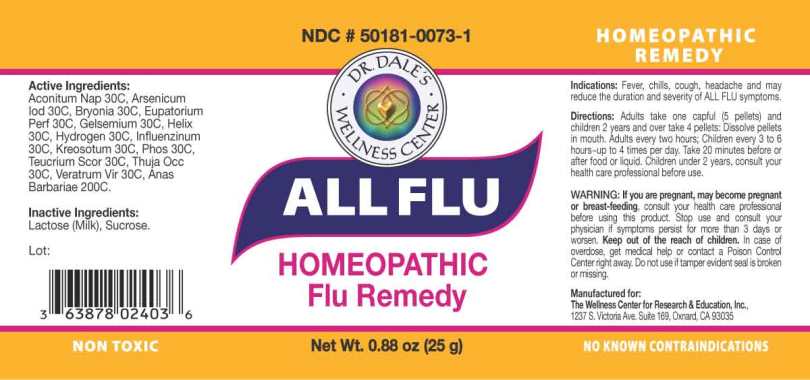 DRUG LABEL: All Flu
NDC: 50181-0073 | Form: PELLET
Manufacturer: The Wellness Center For Research and Education
Category: homeopathic | Type: HUMAN OTC DRUG LABEL
Date: 20250606

ACTIVE INGREDIENTS: ACONITUM NAPELLUS WHOLE 30 [hp_C]/1 g; ARSENIC TRIIODIDE 30 [hp_C]/1 g; BRYONIA ALBA ROOT 30 [hp_C]/1 g; EUPATORIUM PERFOLIATUM FLOWERING TOP 30 [hp_C]/1 g; GELSEMIUM SEMPERVIRENS ROOT 30 [hp_C]/1 g; ESCARGOT SHELL, COOKED 30 [hp_C]/1 g; HYDROGEN 30 [hp_C]/1 g; INFLUENZA A VIRUS A/BRISBANE/02/2018 IVR-190 (H1N1) ANTIGEN (FORMALDEHYDE INACTIVATED) 30 [hp_C]/1 g; INFLUENZA A VIRUS A/KANSAS/14/2017 X-327 (H3N2) ANTIGEN (FORMALDEHYDE INACTIVATED) 30 [hp_C]/1 g; INFLUENZA B VIRUS B/MARYLAND/15/2016 ANTIGEN (FORMALDEHYDE INACTIVATED) 30 [hp_C]/1 g; WOOD CREOSOTE 30 [hp_C]/1 g; PHOSPHORUS 30 [hp_C]/1 g; TEUCRIUM SCORODONIA FLOWERING TOP 30 [hp_C]/1 g; THUJA OCCIDENTALIS LEAFY TWIG 30 [hp_C]/1 g; VERATRUM VIRIDE ROOT 30 [hp_C]/1 g; CAIRINA MOSCHATA HEART/LIVER AUTOLYSATE 200 [hp_C]/1 g
INACTIVE INGREDIENTS: SUCROSE

Drug Facts:

ACTIVE INGREDIENTS:

Aconitum Napellus 30C, Arsenicum Iodatum 30C, Bryonia (Alba) 30C, Eupatorium Perfoliatum 30C, Gelsemium Sempervirens 30C, Helix Tosta 30C, Hydrogen 30C, Influenzinum (2019-2020) 30C, Kreosotum 30C, Phosphorus 30C, Teucrium Scorodonia 30C, Thuja Occidentalis 30C, Veratrum Viride 30C, Anas Barbariae, Hepatis Et Cordis Extractum 200C.

INDICATIONS:

Fever, chills, cough, headache and may reduce the duration and severity of ALL FLU symptoms.

WARNINGS:

If you are pregnant, may become pregnant or breastfeeding, consult your health care professional before using this product.

Stop use and consult your physician if symptoms persist for more than 3 days or worsen.

Keep out of the reach of children. In case of overdose, get medical help or contact a Poison Control Center right away.

Do not use if tamper evident seal is broken or missing.

KEEP OUT OF REACH OF CHILDREN:

Keep out of the reach of children. In case of overdose, get medical help or contact a Poison Control Center right away.

DIRECTIONS:

Adults take one capful (5 pellets) and children 2 years and over take 4 pellets:

Dissolve pellets in mouth. Adults every two hours; Children every 3 to 6 hours~up to 4 times per day.

Take 20 minutes before or after food or liquid.

Children under 2 years, consult your health care professional before use.

INDICATIONS:

Fever, chills, cough, headache and may reduce the duration and severity of ALL FLU symptoms.

INACTIVE INGREDIENTS:

Sucrose, Lactose

QUESTIONS:

Manufactured for:

The Wellness Center for Research and Education, Inc.,

1237 S. Victoria Ave. Suite 169 Oxnard, CA 93035

PACKAGE LABEL DISPLAY:

NDC # 50181-0073-1 HOMEOPATHIC REMEDY

DR. DALE'S

WELLNESS CENTER

ALL FLU

HOMEOPATHIC

Flu Remedy

NON TOXIC Net Wt. .88 oz (25g) NO KNOWN CONTRADICTIONS